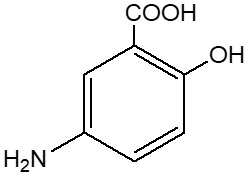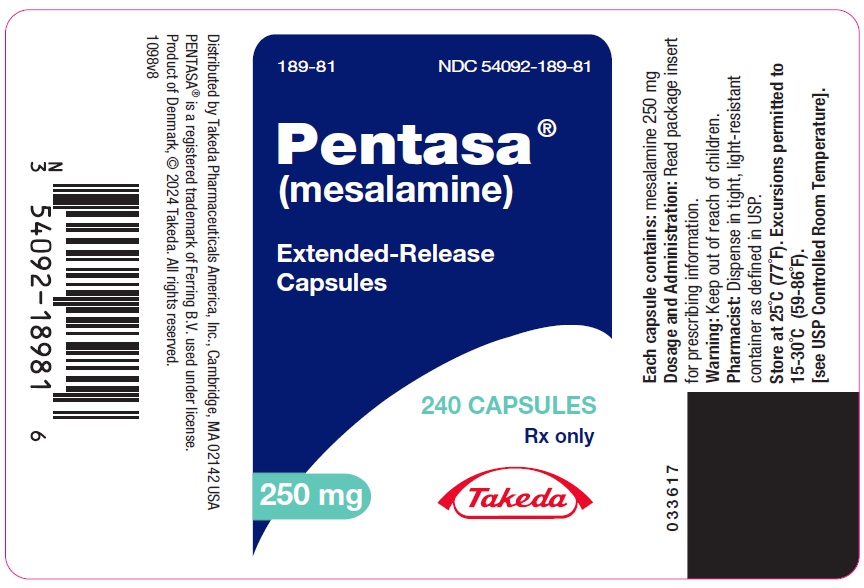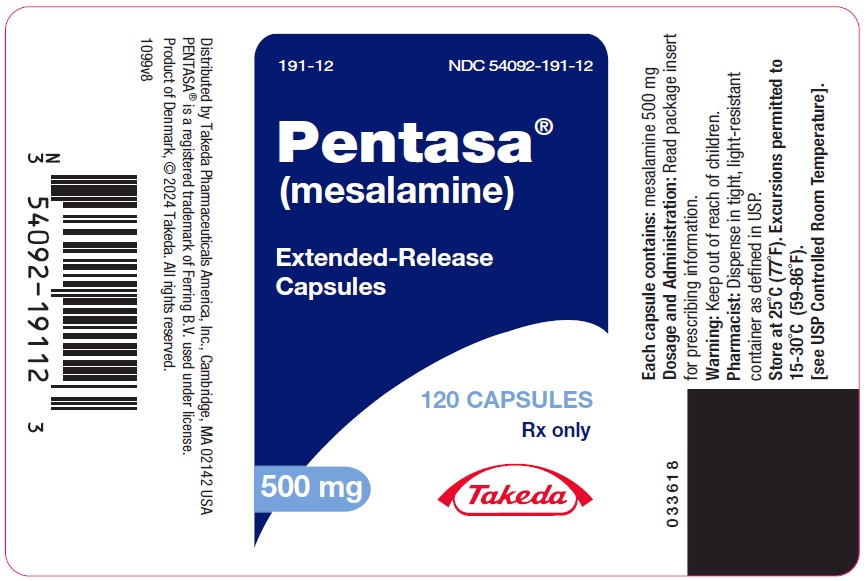 DRUG LABEL: Pentasa
NDC: 54092-189 | Form: CAPSULE
Manufacturer: Takeda Pharmaceuticals America, Inc.
Category: prescription | Type: HUMAN PRESCRIPTION DRUG LABEL
Date: 20250115

ACTIVE INGREDIENTS: MESALAMINE 250 mg/1 1
INACTIVE INGREDIENTS: DIACETYLATED MONOGLYCERIDES; CASTOR OIL; SILICON DIOXIDE; ETHYLCELLULOSE, UNSPECIFIED; HYPROMELLOSE, UNSPECIFIED; STEARIC ACID; SUCROSE; TALC; WHITE WAX; D&C YELLOW NO. 10; FD&C BLUE NO. 1; FD&C GREEN NO. 3; GELATIN, UNSPECIFIED; TITANIUM DIOXIDE

HIGHLIGHTS OF PRESCRIBING INFORMATION

These highlights do not include all the information needed to use PENTASA safely and effectively. See full prescribing information for PENTASA.
PENTASA® (mesalamine) extended-release capsules, for oral use
Initial U.S. Approval: 1987

1 INDICATIONS AND USAGE

PENTASA is an aminosalicylate indicated for the induction of remission and for the treatment of mildly to moderately active ulcerative colitis in adult patients. (1)

2 DOSAGE AND ADMINISTRATION

- Evaluate renal function prior to initiation of PENTASA and periodically while on therapy. (2, 5.1)
- The recommended dosage is 1 g administered orally four times daily. (2)
- Swallow capsules whole; do not crush or chew. (2)
- Alternatively, the capsule(s) may be opened and the contents sprinkled onto applesauce or yogurt. (2)
- Drink an adequate amount of fluids. (2, 5.7)

3 DOSAGE FORMS AND STRENGTHS

Extended-release capsules: 250 mg and 500 mg. (3)

4 CONTRAINDICATIONS

Known or suspected hypersensitivity to salicylates or aminosalicylates or to any of the ingredients of PENTASA. (4, 5.3)

5 WARNINGS AND PRECAUTIONS

- Renal Impairment: Assess renal function at the beginning of treatment and periodically during treatment. Evaluate the risks and benefits of PENTASA in patients with known renal impairment or taking nephrotoxic drug. Discontinue PENTASA if renal function deteriorates while on therapy. (5.1, 7.1, 8.6)
- Mesalamine-Induced Acute Intolerance Syndrome: Discontinue treatment if acute intolerance syndrome (cramping, acute abdominal pain, bloody diarrhea, sometimes fever, headache and rash) is suspected. (5.2)
- Hypersensitivity Reactions, including myocarditis and pericarditis: Discontinue PENTASA if a hypersensitivity reaction is suspected. (5.3)
- Hepatic Failure: Evaluate the risks and benefits of using PENTASA in patients with known liver impairment. (5.4)
- Severe Cutaneous Adverse Reactions: Discontinue at the first signs or symptoms of severe cutaneous adverse reactions or other signs of hypersensitivity and consider further evaluation. (5.5)
- Photosensitivity: Avoid sun exposure if pre-existing skin conditions. (5.6)
- Nephrolithiasis: Cases of nephrolithiasis have been reported with the use of mesalamine. Mesalamine-containing stones are undetectable by standard radiography or computed tomography (CT). Ensure adequate hydration during treatment. (5.7)
- Interference with Laboratory Tests: Mesalamine may lead to elevated urinary normetanephrine test results. (5.8)

6 ADVERSE REACTIONS

Most common adverse reactions are nausea and vomiting (1%). (6.1)

To report SUSPECTED ADVERSE REACTIONS, contact Takeda Pharmaceuticals U.S.A., Inc. at 1-877-TAKEDA-7 (1-877-825-3327) or FDA at 1-800-FDA-1088 or www.fda.gov/medwatch.

7 DRUG INTERACTIONS

- Nephrotoxic Agents including Non-Steroidal Anti-inflammatory Drugs (NSAIDs): Increased risk of nephrotoxicity; monitor for changes in renal function and mesalamine-related adverse reactions. (7.1)
- Azathioprine or 6-Mercaptopurine: Increased risk of blood dyscrasias; monitor complete blood cell counts and platelet counts. (7.2)

8 USE IN SPECIFIC POPULATIONS

Geriatric Patients: Increased risk of blood dyscrasias; monitor complete blood cell counts and platelet counts. (8.5)

FULL PRESCRIBING INFORMATION

1 INDICATIONS AND USAGE

PENTASA is indicated for the induction of remission and for the treatment of mildly to moderately active ulcerative colitis in adult patients.

2 DOSAGE AND ADMINISTRATION

Evaluate renal function prior to initiation of PENTASA and periodically while on therapy [see Warnings and Precautions (5.1)].

Recommended Dosage

The recommended dosage for the induction of remission and the symptomatic treatment of mildly to moderately active ulcerative colitis in adults is 1 g (4 PENTASA 250 mg capsules or 2 PENTASA 500 mg capsules) administered orally four times daily.

Administration Instructions

- Swallow PENTASA capsules whole; do not crush or chew.
- Alternatively, the capsule(s) may be opened and the entire contents sprinkled onto applesauce or yogurt. Consume the entire mixture immediately.
- Drink an adequate amount of fluids during treatment [see Warnings and Precautions (5.7)].

3 DOSAGE FORMS AND STRENGTHS

Extended-release capsules

- 250 mg as a green and blue capsule imprinted with a pentagonal starburst logo and the number 2010 on the green portion of the capsule and S429 250 mg on the blue portion of the capsule.
- 500 mg as a blue capsule imprinted with a pentagonal starburst logo and S429 500 mg.

4 CONTRAINDICATIONS

PENTASA is contraindicated in patients with known or suspected hypersensitivity to salicylates, aminosalicylates, or any ingredients of PENTASA [see Warnings and Precautions (5.3)].

5 WARNINGS AND PRECAUTIONS

5.1 Renal Impairment

Renal impairment, including minimal change disease, acute and chronic interstitial nephritis, and renal failure have been reported in patients given PENTASA or other products that contain mesalamine or are converted to mesalamine.

Evaluate the risks and benefits of using PENTASA in patients with known renal impairment or a history of renal disease or taking concomitant nephrotoxic drugs. Evaluate renal function in all patients prior to initiation and periodically while on therapy with PENTASA. Discontinue PENTASA if renal function deteriorates while on therapy [see Drug Interactions (7.1), Use in Specific Populations (8.6)].

5.2 Mesalamine-Induced Acute Intolerance Syndrome

Mesalamine has been associated with an acute intolerance syndrome that may be difficult to distinguish from an exacerbation of ulcerative colitis. Symptoms include cramping, acute abdominal pain, bloody diarrhea, and sometimes fever, headache, and rash. Monitor patients for worsening of these symptoms while on treatment. If acute intolerance syndrome is suspected, promptly discontinue treatment with PENTASA.

5.3 Hypersensitivity Reactions

Hypersensitivity reactions have been reported in patients taking sulfasalazine. Some patients may have a similar reaction to PENTASA or to other compounds that contain or are converted to mesalamine.

As with sulfasalazine, mesalamine-induced hypersensitivity reactions may present as internal organ involvement, including myocarditis, pericarditis, nephritis, hepatitis, pneumonitis, and hematologic abnormalities. Evaluate patients immediately if signs or symptoms of a hypersensitivity reaction are present. Discontinue PENTASA if an alternative etiology for the signs and symptoms cannot be established.

5.4 Hepatic Failure

There have been reports of hepatic failure in patients with pre-existing liver disease who have been administered other products containing mesalamine. Evaluate the risks and benefits of using PENTASA in patients with known liver impairment.

5.5 Severe Cutaneous Adverse Reactions

Severe cutaneous adverse reactions, such as Stevens-Johnson syndrome (SJS) and toxic epidermal necrolysis (TEN), drug reaction with eosinophilia and systemic symptoms (DRESS), and acute generalized exanthematous pustulosis (AGEP) have been reported in with the use of mesalamine [see Adverse Reactions (6.2)]. Discontinue PENTASA at the first signs or symptoms of severe cutaneous adverse reactions or other signs of hypersensitivity and consider further evaluation.

5.6 Photosensitivity

Patients with pre-existing skin conditions such as atopic dermatitis and atopic eczema have reported more severe photosensitivity reactions. Advise patients to avoid sun exposure, wear protective clothing, and use a broad-spectrum sunscreen when outdoors.

5.7 Nephrolithiasis

Cases of nephrolithiasis have been reported with the use of mesalamine, including stones with 100% mesalamine content. Mesalamine-containing stones are radiotransparent and undetectable by standard radiography or computed tomography (CT). Ensure adequate hydration during treatment with PENTASA.

5.8 Interference with Laboratory Tests

Use of mesalamine may lead to spuriously elevated test results when measuring urinary normetanephrine by liquid chromatography with electrochemical detection because of the similarity in the chromatograms of normetanephrine and mesalamine’s main metabolite, N-acetyl-5-aminosalicylic acid (N-Ac-5-ASA). Consider an alternative, selective assay for normetanephrine.

6 ADVERSE REACTIONS

The following clinically significant adverse reactions are described elsewhere in the labeling:

- Renal impairment [see Warnings and Precautions (5.1)]
- Mesalamine-induced acute intolerance syndrome [see Warnings and Precautions (5.2)]
- Hypersensitivity reactions [see Warnings and Precautions (5.3)]
- Hepatic failure [see Warnings and Precautions (5.4)]
- Severe cutaneous adverse reactions [see Warnings and Precautions (5.5)]
- Photosensitivity [see Warnings and Precautions (5.6)]
- Nephrolithiasis [see Warnings and Precautions (5.7)]

6.1 Clinical Trials Experience

Because clinical trials are conducted under widely varying conditions, adverse reaction rates observed in the clinical trials of a drug cannot be directly compared to rates in the clinical trials of another drug and may not reflect the rates observed in practice.

More than 2100 patients were exposed to PENTASA in clinical trials of ulcerative colitis or another gastrointestinal condition. The most common adverse reactions (i.e., greater than or equal to 1%) were diarrhea (3%), headache (2%), nausea (2%), abdominal pain (2%), dyspepsia (2%), vomiting (2%), and rash (1%).

The safety of PENTASA was evaluated in two randomized, double-blind, placebo-controlled, dose-response trials (UC-1 and UC-2) of 624 patients with mildly to moderately active ulcerative colitis for up to 8 weeks of treatment [see Clinical Studies (14)]. The most common adverse reaction was nausea and vomiting: 1% in the PENTASA group (N=451) and 0% in the placebo group (N=173). Withdrawal from therapy due to adverse reactions was 7% in the PENTASA group and 4% in the placebo group.

The following adverse reactions, presented by body system, were reported in less than 1% of patients in UC-1, UC-2, and clinical trials for another gastrointestinal condition.

Blood and lymphatic system disorders: thrombocythemia, thrombocytopenia

Cardiac Disorders: palpitations, pericarditis, vasodilation

Gastrointestinal Disorders: abdominal distention, constipation, duodenal ulcer, dysphagia, eructation, esophageal ulcer, fecal incontinence, GI bleeding, mouth ulcer, pancreatitis, rectal bleeding, stool abnormalities (color or texture change)

General disorders and administration site conditions: fever, malaise

Infections and infestations: oral moniliasis, conjunctivitis

Investigations: GGTP increase, increased alkaline phosphatase, LDH increase, SGOT increase, SGPT increase, lipase increase, amylase increase

Metabolism and nutritional disorders: anorexia, edema, thirst

Musculoskeletal and connective tissue disorders: arthralgia, leg cramps, myalgia

Nervous System Disorders: dizziness, insomnia, somnolence, paresthesia

Psychiatric disorders: depression, asthenia

Renal and urinary disorders: albuminuria, hematuria, urinary frequency

Reproductive system and breast disorders: amenorrhea, breast pain, hypomenorrhea, menorrhagia, metrorrhagia

Respiratory, Thoracic and Mediastinal Disorders: pulmonary infiltrates, one week after completion of an 8-week ulcerative colitis study, a 72-year-old male, with no previous history of pulmonary problems, developed dyspnea. The patient was subsequently diagnosed with interstitial pulmonary fibrosis without eosinophilia by one physician and bronchiolitis obliterans with organizing pneumonitis by a second physician.

Skin and Subcutaneous Tissue Disorders: acne, alopecia, dry skin, eczema, erythema nodosum, nail disorder, photosensitivity, pruritus, sweating, urticaria, ecchymosis, lichen planus

6.2 Postmarketing Experience

The following adverse reactions have been identified during post-approval use of mesalamine. Because these reactions are reported voluntarily from a population of uncertain size, it is not always possible to reliably estimate their frequency or establish a causal relationship to drug exposure.

Cardiac Disorders: chest pain, fatal myocarditis, pericarditis, T-wave abnormalities

Hematologic Disorders: agranulocytosis, anemia, aplastic anemia, leukopenia, pancytopenia

Hepatic Disorders: cirrhosis, jaundice, including cholestatic jaundice; hepatotoxicity, hepatitis, and possible hepatocellular damage including liver necrosis and liver failure. Some of these cases were fatal. One case of Kawasaki-like syndrome which included hepatic function changes was also reported.

Immune System Disorders: anaphylactic reaction, angioedema, lupus-like syndrome, systemic lupus erythematosus

Nervous System Disorders: intracranial hypertension

Renal and Urinary Disorders: acute renal failure, chronic renal failure, interstitial nephritis, nephrogenic diabetes insipidus, nephrolithiasis, nephrotic syndrome [see Warnings and Precautions (5.1, 5.7)]

- Urine discoloration occurring ex-vivo caused by contact of mesalamine, including inactive metabolite, with surfaces or water treated with hypochlorite-containing bleach

Reproductive System and Breast Disorders: reversible oligospermia

Respiratory, Thoracic and Mediastinal Disorders: hypersensitivity pneumonitis (including interstitial pneumonitis, allergic alveolitis, eosinophilic pneumonitis), interstitial lung disease, pleurisy/pleuritis, pneumonitis

Skin and Subcutaneous Tissue Disorders: AGEP, DRESS, SJS/TEN [see Warnings and Precautions (5.5)]

7 DRUG INTERACTIONS

7.1 Nephrotoxic Agents, Including Non-Steroidal Anti-Inflammatory Drugs

The concurrent use of mesalamine with known nephrotoxic agents, including non-steroidal anti-inflammatory drugs (NSAIDs), may increase the risk of nephrotoxicity. Monitor patients taking nephrotoxic drugs for changes in renal function and mesalamine-related adverse reactions [see Warnings and Precautions (5.1)].

7.2 Azathioprine or 6-Mercaptopurine

The concurrent use of mesalamine with azathioprine or 6-mercaptopurine and/or any other drugs known to cause myelotoxicity may increase the risk for blood disorders, bone marrow failure, and associated complications. If concomitant use of PENTASA and azathioprine or 6-mercaptopurine cannot be avoided, monitor blood tests, including complete blood cell counts and platelet counts.

7.3 Interference with Urinary Normetanephrine Measurements

Use of PENTASA may lead to spuriously elevated test results when measuring urinary normetanephrine by liquid chromatography with electrochemical detection [see Warnings and Precautions (5.8)]. Consider an alternative, selective assay for normetanephrine.

8 USE IN SPECIFIC POPULATIONS

8.1 Pregnancy

Risk Summary

Published data from meta-analyses, cohort studies, and case series on the use of mesalamine during pregnancy have not reliably informed an association with mesalamine and major birth defects, miscarriage, or adverse maternal or fetal outcomes (see Data). There are adverse effects on maternal and fetal outcomes associated with ulcerative colitis in pregnancy (see Clinical Considerations).

In animal reproduction studies, oral administration of mesalamine during organogenesis to pregnant rats at doses up to 1000 mg/kg/day (approximately 2.4 times the maximum recommended human dose of 4 g/day, based on a body surface area comparison) and rabbits at doses of 800 mg/kg/day (approximately 3.9 times the maximum recommended human dose of 4 g/day, based on a body surface area comparison) revealed no evidence of adverse developmental effects (see Data).

The background risk of major birth defects and miscarriage for the indicated populations is unknown. All pregnancies have a background risk of birth defect, loss, or other adverse outcomes. In the U.S. general population, the estimated background risk of major birth defects and miscarriages in clinically recognized pregnancies is 2% to 4% and 15% to 20%, respectively.

Clinical Considerations

Disease-associated maternal and embryo/fetal risk

Published data suggest that increased disease activity is associated with the risk of developing adverse pregnancy outcomes in women with ulcerative colitis. Adverse pregnancy outcomes include preterm delivery (before 37 weeks of gestation), low birth weight (less than 2500 g) infants, and small for gestational age at birth.

Data

Human Data

Published data from meta-analyses, cohort studies, and case series on the use of mesalamine during early pregnancy (first trimester) and throughout pregnancy have not reliably informed an association of mesalamine and major birth defects, miscarriage, or adverse maternal or fetal outcomes. There is no clear evidence that mesalamine exposure in early pregnancy is associated with an increased risk of major congenital malformations, including cardiac malformations. Published epidemiologic studies have important methodological limitations which hinder interpretation of the data, including inability to control for confounders, such as underlying maternal disease, maternal use of concomitant medications, and missing information on the dose and duration of use for mesalamine products.

Animal Data

Reproduction studies with mesalamine during organogenesis have been performed in pregnant rats at doses up to 1000 mg/kg/day (approximately 2.4 times the maximum recommended human dose of 4 g/day, based on a body surface area comparison) and rabbits at doses up to 800 mg/kg/day (approximately 3.9 times the maximum recommended human dose of 4 g/day based on a body surface area comparison) and have revealed no evidence of harm to the fetus due to mesalamine.

8.2 Lactation

Risk Summary

Data from published literature report the presence of mesalamine and its metabolite, N-acetyl-5-aminosalicylic acid in human milk in small amounts with relative infant doses (RID) of 0.1% or less for mesalamine (see Data). There are case reports of diarrhea observed in breastfed infants exposed to mesalamine (see Clinical Considerations). There is no information on the effects of mesalamine on milk production. The lack of clinical data during lactation precludes a clear determination of the risk of PENTASA to an infant during lactation; therefore, the developmental and health benefits of breastfeeding should be considered along with the mother’s clinical need for PENTASA and any potential adverse effects on the breastfed child from PENTASA or from the underlying maternal condition.

Clinical Considerations

Advise the caregiver to monitor the breastfed infant for diarrhea.

Data

In published lactation studies, maternal mesalamine doses from various oral and rectal formulations and products ranged from 500 mg to 4.8 g daily. The average concentration of mesalamine in milk ranged from non-detectable to 0.5 mg/L. The average concentration of N-acetyl-5-aminosalicylic acid in milk ranged from 0.2 to 9.3 mg/L. Based on these concentrations, estimated infant daily dosages for an exclusively breastfed infant are 0 to 0.075 mg/kg/day of mesalamine (RID 0% to 0.1%) and 0.03 to 1.4 mg/kg/day of N-acetyl-5-aminosalicylic acid.

8.4 Pediatric Use

Safety and effectiveness in pediatric patients have not been established.

8.5 Geriatric Use

Clinical trials of PENTASA did not include sufficient numbers of patients aged 65 years and over to determine whether they respond differently from younger patients. Reports from uncontrolled clinical studies and postmarketing reporting systems suggested a higher incidence of blood dyscrasias (i.e., agranulocytosis, neutropenia, and pancytopenia) in patients receiving mesalamine-containing products such as PENTASA who were 65 years or older compared to younger adult patients, which may also be associated with ulcerative colitis, use of interacting drugs, or reduced renal function. Monitor complete blood cell counts and platelet counts in patients 65 years and over during treatment with PENTASA.

In general, consider the greater frequency of decreased hepatic, renal, or cardiac function, and of concurrent disease or other drug therapy in patients 65 years and over when prescribing PENTASA.

8.6 Renal Impairment

Mesalamine is known to be substantially excreted by the kidney, and the risk of toxic reactions may be greater in patients with impaired renal function. Evaluate renal function in all patients prior to initiation and periodically while on PENTASA therapy. Monitor patients with known renal impairment or history of renal disease or taking nephrotoxic drugs for decreased renal function and mesalamine-related adverse reactions. Discontinue PENTASA if renal function deteriorates while on therapy [see Warnings and Precautions (5.1), Adverse Reactions (6.2), Drug Interactions (7.1)].

10 OVERDOSAGE

PENTASA is an aminosalicylate, and symptoms of salicylate toxicity may be possible, such as: nausea, vomiting, abdominal pain, tachypnea, hyperpnea, tinnitus, and neurologic symptoms (headache, dizziness, confusion, seizures). Severe intoxication with salicylates may lead to electrolyte and blood pH imbalance and potentially to other organ (e.g., renal and liver) damage.

There is no specific antidote for mesalamine overdose; however, conventional therapy for salicylate toxicity may be beneficial in the event of acute overdosage and may include gastrointestinal tract decontamination to prevent further absorption. Correct fluid and electrolyte imbalance by the administration of appropriate intravenous therapy and maintain adequate renal function.

11 DESCRIPTION

PENTASA (mesalamine) for oral administration is an extended-release formulation of mesalamine, an aminosalicylate anti-inflammatory agent for gastrointestinal use.

Mesalamine (also referred to as 5-aminosalicylic acid or 5-ASA) has the chemical name 5-amino-2-hydroxybenzoic acid. It has a molecular weight of 153.14.

The structural formula is:

Each 250 mg capsule contains 250 mg of mesalamine. It also contains the following inactive ingredients: acetylated monoglyceride, castor oil, colloidal silicon dioxide, ethylcellulose, hydroxypropyl methylcellulose, starch, stearic acid, sugar, talc, and white wax. The capsule shell contains D&C Yellow #10, FD&C Blue #1, FD&C Green #3, gelatin, titanium dioxide, and other ingredients.

Each 500 mg capsule contains 500 mg of mesalamine. It also contains the following inactive ingredients: acetylated monoglyceride, castor oil, colloidal silicon dioxide, ethylcellulose, hydroxypropyl methylcellulose, starch, stearic acid, sugar, talc, and white wax. The capsule shell contains FD&C Blue #1, gelatin, titanium dioxide, and other ingredients.

12 CLINICAL PHARMACOLOGY

12.1 Mechanism of Action

The mechanism of action of mesalamine is not fully understood, but it appears to be a topical anti-inflammatory effect on colonic epithelial cells. Mucosal production of arachidonic acid metabolites, both through the cyclooxygenase pathways (i.e., prostanoids) and through the lipoxygenase pathways (i.e., leukotrienes and hydroxyeicosatetraenoic acids), is increased in patients with ulcerative colitis, and it is possible that mesalamine diminishes inflammation by blocking cyclooxygenase and inhibiting prostaglandin production in the colon.

12.2 Pharmacodynamics

The exposure-response relationship and time course of pharmacodynamic response for the safety and effectiveness of mesalamine have not been fully characterized.

12.3 Pharmacokinetics

Absorption

Following oral administration 20% to 30% of the mesalamine in PENTASA is absorbed based on urinary excretion data.

Plasma mesalamine concentration peaked at approximately 1 mcg/mL 3 hours following a 1 g PENTASA dose.

Oral mesalamine pharmacokinetics were nonlinear when PENTASA capsules were dosed from 250 mg to 1 g four times daily, with steady-state mesalamine plasma concentrations increasing about nine times, from 0.14 mcg/mL to 1.21 mcg/mL.

The major metabolite of mesalamine (5-aminosalicylic acid), N-acetyl-5-aminosalicylic acid, peaked at approximately 3 hours at 1.8 mcg/mL. N-acetyl-5-aminosalicylic acid pharmacokinetics were linear.

Distribution

Mesalamine is approximately 43% bound to plasma proteins at the concentration of 2.5 mcg/mL.

Elimination

Metabolism

The greater than dose proportional increase in PK of mesalamine suggests saturable first pass metabolism. The major metabolite of mesalamine, N-acetyl-5-aminosalicylic acid, is formed due to action of N-acetyltransferase in the liver and intestinal mucosa. Pharmacological activities of N-acetyl-5-aminosalicylic acid are unknown, and other metabolites have not been identified.

Excretion

Following oral administration, plasma mesalamine concentration declined in a biphasic manner after reaching peak concentration. The literature describes a mean terminal half-life of 42 minutes for mesalamine following intravenous administration. Because of the continuous release and absorption of mesalamine from PENTASA throughout the gastrointestinal tract, the true elimination half-life cannot be determined after oral administration.

N-acetyl-5-aminosalicylic acid was the primary compound excreted in the urine (19% to 30%) following PENTASA dosing. About 130 mg free mesalamine was recovered in the feces following a single 1g PENTASA dose. Elimination of free mesalamine and salicylates in feces increased proportionately with PENTASA dose.

13 NONCLINICAL TOXICOLOGY

13.1 Carcinogenesis, Mutagenesis, Impairment of Fertility

Carcinogenesis

In a 104-week dietary carcinogenicity study of mesalamine, CD-1 mice were administered doses up to 2500 mg/kg/day and it was not tumorigenic. The 2500 mg/kg/day dose represents approximately 2.5 times the maximum recommended human dose on a body surface area basis. In a 104-week dietary carcinogenicity study in Wistar rats, mesalamine up to a dose of 800 mg/kg/day was not tumorigenic. This dose represents approximately 1.5 times the maximum recommended human dose on a body surface area basis.

Mutagenesis

No evidence of mutagenicity was observed in an in vitro Ames test and in an in vivo mouse micronucleus test.

Impairment of Fertility

No effects on fertility or reproductive performance were observed in male or female rats at oral doses of mesalamine up to 400 mg/kg/day (0.8 times the maximum recommended human dose based on body surface area).

14 CLINICAL STUDIES

In two randomized, double-blind, placebo-controlled, dose-response trials (UC-1 and UC-2) of 625 patients with active mild to moderate ulcerative colitis, PENTASA, at an oral dose of 1 g administered four times a day for up to 8 weeks, produced consistent improvement in prospectively identified primary efficacy parameters, Physical Global Assessment, Treatment Failure, and Sigmoidoscopic Index as shown in Table 2.

A PENTASA dosage regimen of 1 g four times a day demonstrated consistent improvement in secondary efficacy parameters, namely the frequency of trips to the toilet, stool consistency, rectal bleeding, abdominal/rectal pain, and urgency. A PENTASA dosage regimen of 1 g four times a day also induced remission as assessed by endoscopic and symptomatic endpoints.

Table 2: Efficacy Parameters in Adults Patients with Mildly to Moderately Active Ulcerative Colitis in Placebo-Controlled, Dose-Response Trials (UC-1 and UC-2)
Parameter Evaluated | Clinical Trial UC-1 |  | Clinical Trial UC-2
Parameter Evaluated | Placebo N=90 | PENTASA 1 g four times a day N=95 | Placebo N=83 | PENTASA 1 g four times a day N=85
Physician Global Assessment^1 | 36% | 59% [p<0.05 vs placebo.] | 31% | 55%
Treatment Failure^2 | 22% | 9% | 31% | 9%
Sigmoidoscopic Index^3 | -2.5 | -5.0 | -1.6 | -3.8
Remission^4 | 12% | 26% | 12% | 27%
^1 proportion of patients with complete or marked improvement.
^2 proportion of patients developing severe or fulminant UC requiring steroid therapy or hospitalization or worsening of the disease at 7 days of therapy, or lack of significant improvement by 14 days of therapy.
^3 an objective measure of disease activity rated by a standard (15-point) scale that includes mucosal vascular pattern, erythema, friability, granularity/ulcerations, and mucopus: improvement over baseline.
^4 defined as complete resolution of symptoms plus improvement of endoscopic endpoints. To be considered in remission, patients had a “1” score for one of the endoscopic components (mucosal vascular pattern, erythema, granularity, or friability) and “0” for the others.

16 HOW SUPPLIED/STORAGE AND HANDLING

PENTASA (mesalamine) extended-release capsules are supplied as shown in the table:

Strength | Description | Supplied As | NDC Number
250 mg extended-release capsules | green and blue capsule with a pentagonal starburst logo and the number 2010 on the green portion of the capsule and S429 250 mg on the blue portion of the capsule | bottles of 240 capsules | NDC 54092-189-81
500 mg extended-release capsules | blue capsule with a pentagonal starburst logo and S429 500 mg on the capsule | bottles of 120 capsules | NDC 54092-191-12

STORAGE AND HANDLING

Store at 25°C (77°F); excursions permitted to 15°C to 30°C (59°F to 86°F) [see USP Controlled Room Temperature].

17 PATIENT COUNSELING INFORMATION

Renal Impairment

Inform patients that PENTASA may decrease their renal function, especially if they have known renal impairment or are taking nephrotoxic drugs, and periodic monitoring of renal function will be performed while they are on therapy. Advise patients to complete all blood tests ordered by their healthcare provider [see Warnings and Precautions (5.1)].

Mesalamine-Induced Acute Intolerance Syndrome and Other Hypersensitivity Reactions

Instruct patients to stop taking PENTASA and report to their healthcare provider if they experience new or worsening symptoms of acute intolerance syndrome (cramping, abdominal pain, bloody diarrhea, fever, headache, and rash) or other symptoms suggestive of mesalamine-induced hypersensitivity [see Warnings and Precautions (5.2, 5.3)].

Hepatic Failure

Advise patients with known liver disease to contact their healthcare provider if they experience signs or symptoms of worsening liver function [see Warnings and Precautions (5.4)].

Severe Cutaneous Adverse Reactions

Inform patients of the signs and symptoms of severe cutaneous adverse reactions. Instruct patients to stop taking PENTASA and report to their healthcare provider at first appearance of a severe cutaneous adverse reaction or other sign of hypersensitivity [see Warnings and Precautions (5.5)].

Photosensitivity

Advise patients with pre-existing skin conditions to avoid sun exposure, wear protective clothing, and use a broad-spectrum sunscreen when outdoors [see Warnings and Precautions (5.6)].

Nephrolithiasis

Instruct patients to drink an adequate amount of fluids during treatment in order to minimize the risk of kidney stone formation and to contact their healthcare provider if they experience signs or symptoms of a kidney stone (e.g., severe side or back pain, blood in the urine) [see Warnings and Precautions (5.7)].

Blood Disorders

Inform elderly patients and those taking azathioprine or 6-mercaptopurine of the risk for blood disorders and the need for periodic monitoring of complete blood cell counts and platelet counts while on therapy. Advise patients to complete all blood tests ordered by their healthcare provider [see Drug Interactions (7.2), Use in Specific Populations (8.5)].

Administration

Instruct patients:

- Swallow PENTASA capsules whole; do not crush or chew.
- Alternatively, the capsule(s) may be opened and the contents sprinkled onto applesauce or yogurt.
- Urine may become discolored reddish-brown while taking PENTASA when it comes in contact with surfaces or water treated with hypochlorite-containing bleach. If discolored urine is observed, advise patients to observe their urine flow. Report to the healthcare provider only if urine is discolored on leaving the body, before contact with any surface or water (e.g., in the toilet).
- Drink an adequate amount of fluids [see Dosage and Administration (2), Warnings and Precautions (5.7)].

Distributed by:
Takeda Pharmaceuticals America, Inc.
Cambridge, MA 02142, USA

PENTASA® is a registered trademark of Ferring B.V. used under license.

© 2024 Takeda Pharmaceuticals U.S.A., Inc. All rights reserved.

Rev. 7/2024

PRINCIPAL DISPLAY PANEL - 250 mg Capsule Bottle Label

189-81
NDC 54092-189-81

Pentasa®
(mesalamine)

Extended-Release
Capsules

240 CAPSULES

Rx only

250 mg

Takeda

PRINCIPAL DISPLAY PANEL - 500 mg Capsule Bottle Label

191-12
NDC 54092-191-12

Pentasa®
(mesalamine)

Extended-Release
Capsules

120 CAPSULES

Rx only

500 mg

Takeda